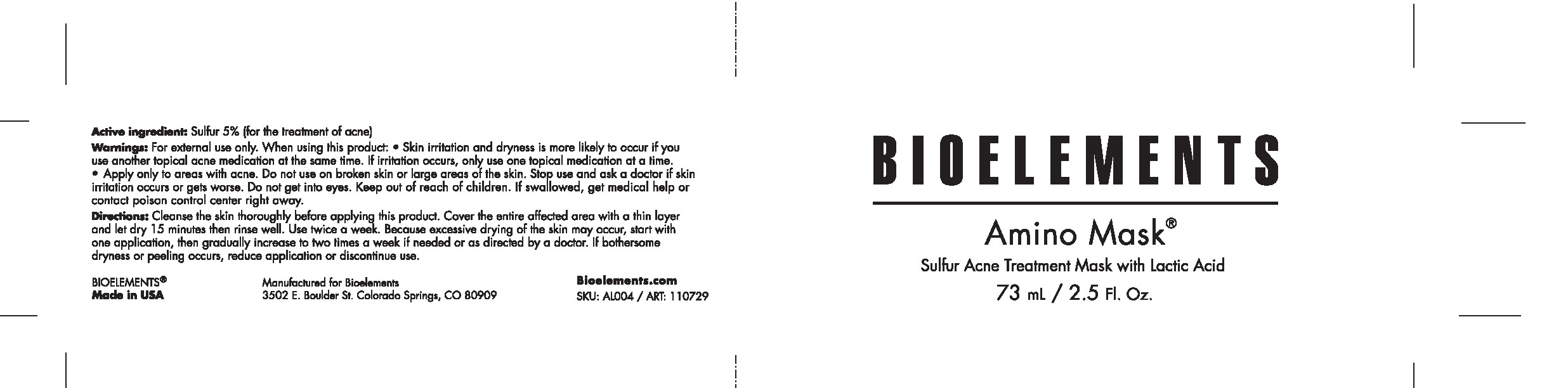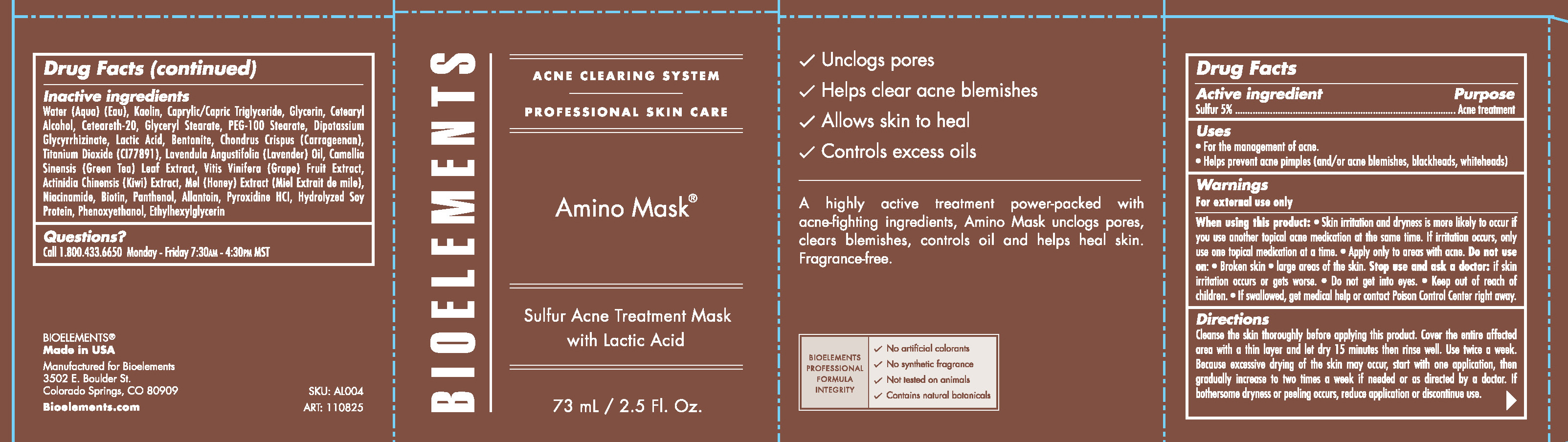 DRUG LABEL: Bioelements
NDC: 49825-123 | Form: CREAM
Manufacturer: Bioelements
Category: otc | Type: HUMAN OTC DRUG LABEL
Date: 20120426

ACTIVE INGREDIENTS: SULFUR 5 mL/100 mL
INACTIVE INGREDIENTS: WATER; KAOLIN; CAPRYLIC/CAPRIC ACID; GLYCERIN; CETOSTEARYL ALCOHOL; POLYOXYL 20 CETOSTEARYL ETHER; GLYCERYL MONOSTEARATE; PEG-100 STEARATE; GLYCYRRHIZINATE DIPOTASSIUM; LACTIC ACID; BENTONITE; CHONDRUS CRISPUS; TITANIUM DIOXIDE; LAVENDER OIL; GREEN TEA LEAF; WINE GRAPE; KIWI FRUIT; HONEY; NIACINAMIDE; BIOTIN; PANTHENOL; ALLANTOIN; PHENOXYETHANOL; ETHYLHEXYLGLYCERIN

Amino Mask

Active ingredients Purpose

Sulfur 5% Acne treatment

Uses

For the management of acne

Helps prevent acne pimples (and/or acne blemishes, blackheads, whiteheads)

Keep out of reach of children

Stop use and ask a doctor

If skin irritation occurs or gets worse

Do not get into eyes

Warnings

For external use only

When using this product:

Skin irritation and dryness is more likely to occur if you use another topical acne medication at the same time. If irritation occurs only use one topical medication at a time.

Apply only to areas with acne

Do not use on:

- Broken Skin

- Large areas of the skin

If swallowed, get medical help or contact a Poison Control Center right away.

Directions

Cleanse the Skin thoroughly before applying this product. Cover the entire affected area with a thin layer and let dry 15 minutes then rinse well. Use twice a week. Because excessive drying of the skin may occur, start with one application, then gradually increase to two times a week if needed or as directed by a doctor. If bothersome dryness or peeling occurs, reduce application or discontinue use.

Inactive ingredients
Water (Aqua) (Eau), Kaolin, Caprylic/Capric Triglyceride, Glycerin, Cetearyl Alcohol, Ceteareth-20, Glyceryl Stearate, PEG-100 Stearate, Dipotassium Glycyrrhizate, Lactic Acid, Bentonite, Chondrus Crispus (Carrageenan), Titanium Dioxide (CI 77891), Lavendula Angustifolia (Lavender) Oil, Camellia Sinensis (Green Tea) Leaf Extract, Vitis Vinifera (Grape) Fruit Extract, Actinidia Chinensis (Kiwi) Extract, Mel (Honey) Extract (Miel Extrait de Mile), Niacinamide, Biotin, Panthenol, Allantoin, Pyroxidine HCL, Hydrolyzed Soy Protein, Phenoxyethanol, Ethylhexylglycerin.

PACKAGE LABEL

Bioelements

Amino Mask (R)

Sulfur Acne Treatment Mask with Lactic Acid

73 mL / 2.5 Fl. Oz.